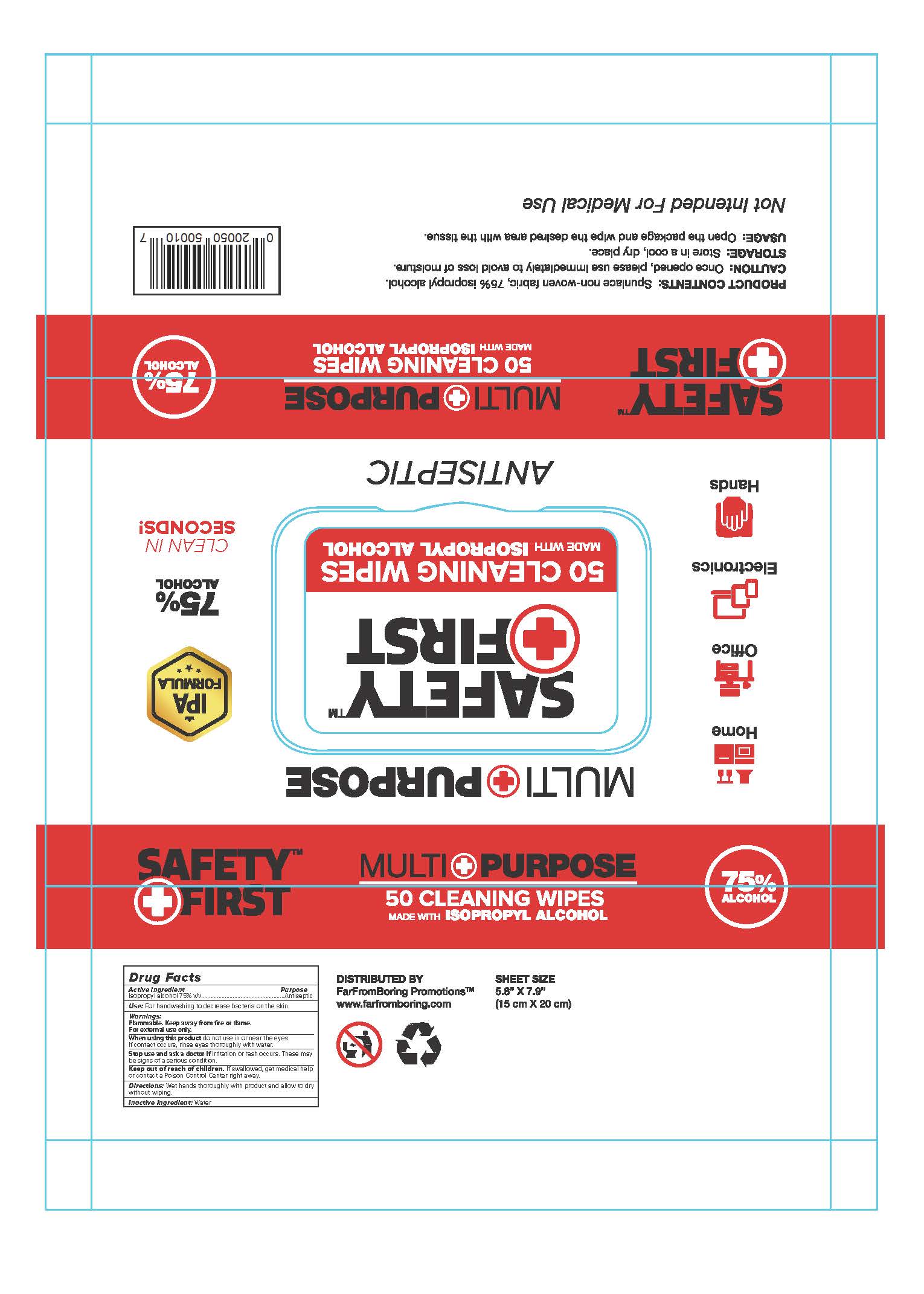 DRUG LABEL: ISOPROPYL ALCOHOL WIPES
NDC: 75163-303 | Form: CLOTH
Manufacturer: Zhuji Jianhe Paper Co., Ltd
Category: otc | Type: HUMAN OTC DRUG LABEL
Date: 20201025

ACTIVE INGREDIENTS: ISOPROPYL ALCOHOL 4.2 mL/1 1
INACTIVE INGREDIENTS: WATER

JianHe-SafetyFirst, Wipes, Isopropyl Alcohol 75% v/v

Active Ingredient

Isopropyl Alcohol 75% v/v. Purpose: Antiseptic

Purpose

Antiseptic, Handwashing wipes

Use

For handwashing to decrease bacteria on the skin.

Warnings

Flammable. Keep away from fire or flame.

For external use only.

Do not use

- in children less than 2 months of age
- on open skin wounds

When using this product do not use in or near the eyes.

If contact occurs, rinse eyes thoroughly with water.

Stop use and ask a doctor if irritation or rash occurs. These may be signs of a serious condition.

Keep out of reach of children. If swallowed, get medical help or contact a Poison Control Center right away.

Directions

Wet hands thoroughly with product and allow to dry without wiping.

Other information

PRODUCT CONTENTS: Spunlace non-woven fabric, 75% isopropyl alcohol.

CAUTION: Once opened, please use immediately to avoid loss of moisture.

STORAGE: Store in a cool, dry place.

USAGE: Open the package and wipe the desired area with the tissue.

Not Intended For Medical Use

Inactive Ingredient

Water

Package Label - Principal Display Panel

Wipes *50 (15*20)

NDC: 75163-303-25